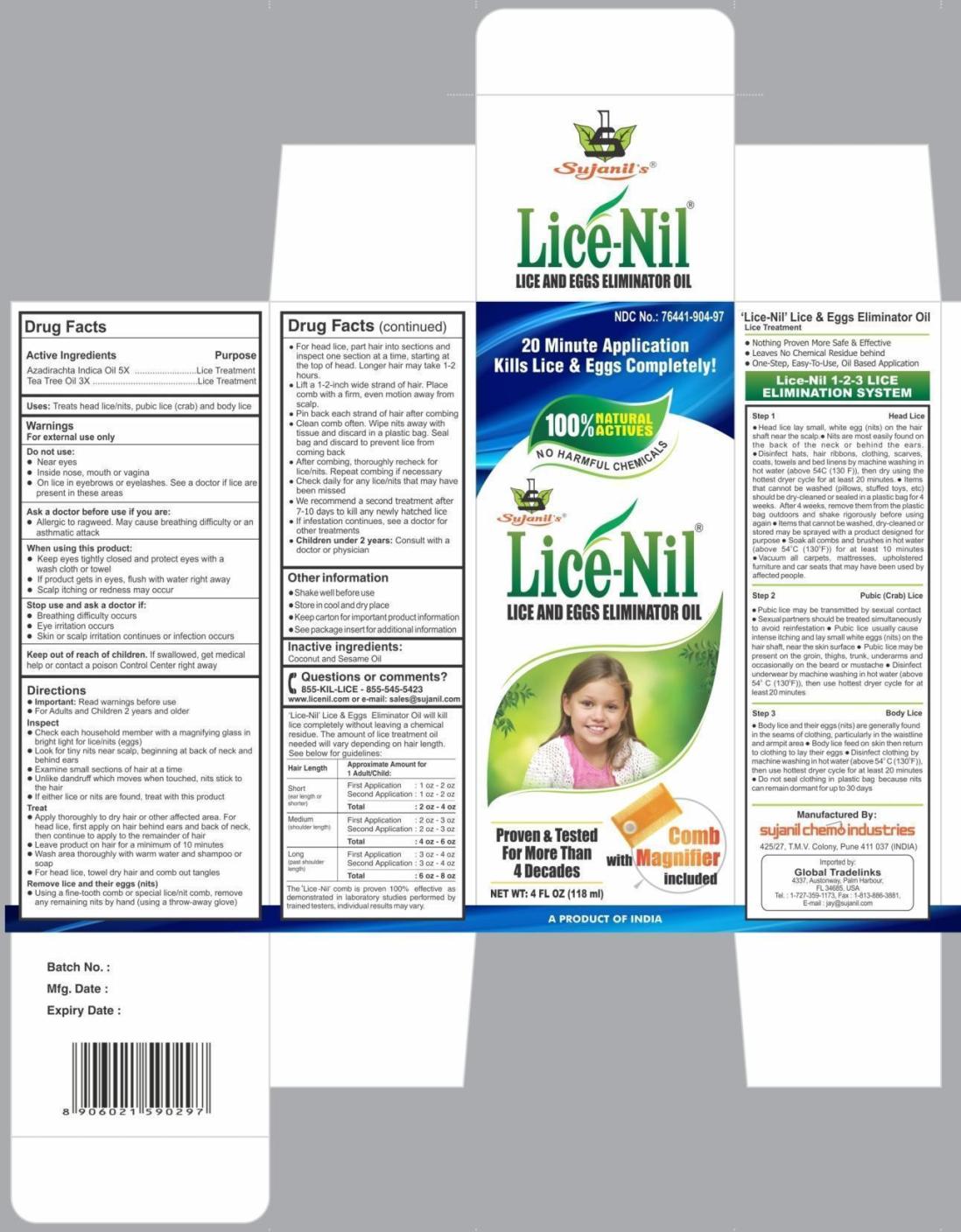 DRUG LABEL: Lice-Nil

NDC: 76441-904 | Form: OIL
Manufacturer: Sujanil Chemo Industries
Category: homeopathic | Type: HUMAN OTC DRUG LABEL
Date: 20150801

ACTIVE INGREDIENTS: AZADIRACHTA INDICA SEED OIL 5 [hp_X]/100 mL; TEA TREE OIL 3 [hp_X]/100 mL
INACTIVE INGREDIENTS: SESAME OIL; COCONUT OIL

Lice-Nil Lice and Eggs Eliminator Oil

Drug Facts

Active ingredients

Azadirachta Indica Oil 5x

Tea Tree Oil 3x

Purpose

Lice Treatment

Uses

treats head lice/nits, pubic lice (crab), and body lice

Warnings

For external use only

Do not use

- near eyes
- inside nose, mouth, or vagina
- on lice in eyebrows or eyelashes. See a doctor if lice are present in these areas.

Ask a doctor before use if you are:

- allergic to ragweed. May cause breathing difficulty or an asthmatic attack.

When using this product

- keep eyes tightly closed and protect eyes with a wash cloth or towel.
- if product gets into eyes, flush with water right away.
- scalp itching or redness may occur.

Stop use and ask a doctor if

- breathing difficulty occurs
- eye irritation occurs
- skin or scalp irritation continues or infection occurs

Keep out of reach of children. If swallowed, get medical help or contact a Poison Control Center right away.

Directions

- Important: Read warnings before use

- for adults and children 2 years and older:

Inspect

- check each household member with a magnifying glass in bright light for lice/nits (eggs)
- look for tiny nits near scalp, beginning at back of neck and behind ears
- examine small sections of hair at a time
- unlike dandruff which moves when touched, nits stick to the hair
- if either lice or nits are found, treat with this product

Treat

- apply thoroughly to dry hair or other affected area. For head lice, first apply on hair behind ears and back of neck, then continue to apply to the remainder of hair.
- leave product on hair for a minimum of 10 minutes.
- wash area thoroughly with warm water and shampoo or soap.
- for head lice, towel dry hair and comb out tangles.

Remove lice and their eggs (nits)

- using a fine-tooth comb or special lice/nit comb, remove any remaining nits by hand (using a throw-away glove).
- for head lice, part hair into sections and inspect one section at a time, starting at the top of head. Longer hair may take 1-2 hours.
- lift a 1- to 2- inch wide strand of hair. Place comb with a firm, even motion away from scalp.
- pin back each strand of hair after combing.
- clean comb often. Wipe nits away with tissue and discard in a plastic bag. Seal bag and discard to prevent lice from coming back.
- after combing, thoroughly recheck for lice/nits. Repeat combing if necessary.
- check daily for any lice/nits that may have been missed.
- we recommend a second treatment after 7 to 10 days to kill any newly hatched lice.
- if infestation continues, see a doctor for other treatments.
- children under 2 years: consult with a doctor or physician

Other Information

- shake well before use
- store in cool and dry place
- keep carton for important product information
- see package insert for additional information.

Inactive ingredients

coconut and sesame oils

Questions or comments?

855-KIL-LICE - 855-545-5423
www.licenil.com or e-mail: sales@sujanil.com

'Lice-Nil' Lice & Eggs Eliminator Oil will kill lice completely without leaving a chemical residue. The amount of lice treatment oil needed will vary depending on hair length.

See below for guidelines:

Usage Guidelines
Hair Length | Approximate Amount for 1 Adult/Child:
Short (ear length or shorter) | First Application : 1 oz - 2 oz; Second Application : 1 oz - 2 oz; Total : 2 oz - 4 oz
Medium (shoulder length) | First Application : 2 oz - 3 oz; Second Application : 2 oz - 3 oz; Total : 4 oz - 6 oz
Long (past shoulder length) | First Application : 3 oz - 4 oz; Second Application : 3 oz - 4 oz; Total : 6 oz - 8 oz

The 'Licel-Nil' comb is proven 100% effective as demonstrated in laboratory studies performed by trained testers, individual results may vary.

'Lice-Nil' Lice & Eggs Eliminator Oil

Lice Treatment

- Nothing Proven More Safe & Effective
- Leaves No Chemical Residue Behind
- One-Step, Easy-To-Use, Oil Based Application

Lice-Nil 1-2-3 LICE ELIMINATION SYSTEM

Step 1 Head Lice

- Head lice lay small white eggs (nits) on hair shaft close to the scalp
- Nits are most easily found on the back of the neck or behind the ears
- Disinfect hats, hair ribbons, clothing, scarves, coats, towels and bed linens by machine washing in hot water (above 54°C (130°F)), then dry using the hottest dryer cycle for at least 20 minutes
- Items that cannot be washed (pillows, stuffed toys, etc.) should be dry-cleaned or sealed in a plastic bag for 4 weeks. After 4 weeks, remove them from the plastic bag outdoors and shake rigorously before using again
- Items that cannot be washed, dry-cleaned, or stored may be sprayed with a product designed for purpose
- Soak all combs and brushes in hot water (above 54°C (130°F)) for at least 10 minutes
- Vacuum all carpets, mattresses, upholstered furniture, and car seats that may have been used by affected people.

Step 2 Pubic (Crab) Lice

- Pubic Lice may be transmitted by sexual contact.
- Sexual partners should be treated simultaneously to avoid reinfestation.
- Pubic Lice usually cause intense itching and lay small white eggs (nits) on the hair shaft near the skin surface.
- Pubic Lice may be present on the groin, thighs, trunk, underarms and occasionally on the beard and mustache.
- Disinfect underwear by machine washing in hot water (above 54°C (130°F)), then use hottest dryer cycle for at least 20 minutes.

Step 3 Body Lice

- Body Lice and their eggs (nits) are generally found in the seams of clothing particularly in the waistline and armpit area.
- Body Lice feed on skin then return to clothing to lay their eggs.
- Disinfect clothing by machine washing in hot water (above 54°C (130°F)), then use hottest dryer cycle for at least 20 minutes.
- Do not seal clothing in plastic bag because nits can remain dormant for up to 30 days.

Principal Display Panel

NDC No.: 76441-904-97

Sujanil's

Lice-Nil

Lice and Eggs Eliminator Oil

Proven and tested for more than 4 Decades

Comb with Magnifier Included

Manufactured By:

Sujanil Chemo Industries

425/27, T.M.V Colony,

Pune - 411 037 (INDIA)